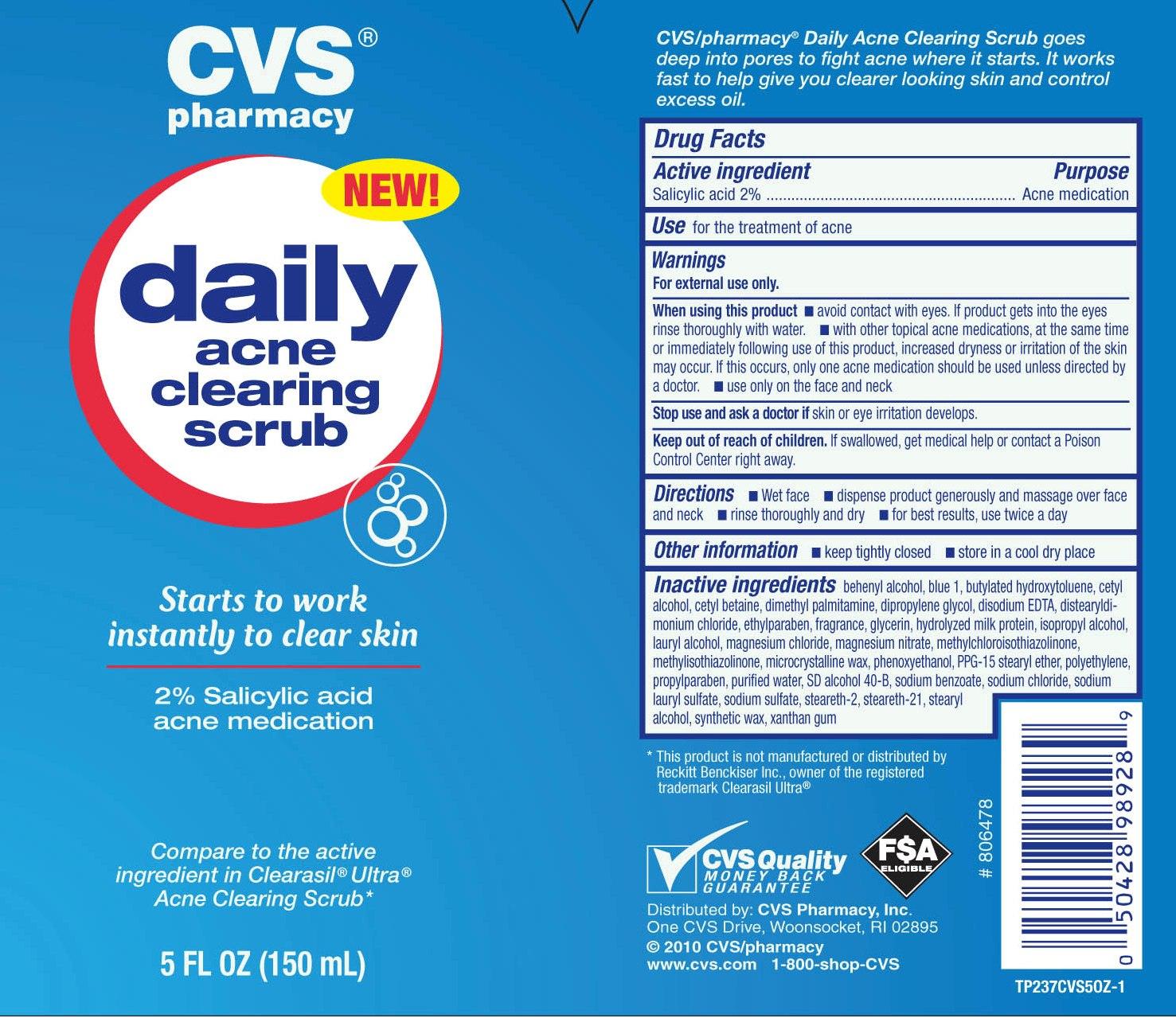 DRUG LABEL: CVS Daily Acne Clearing Scrub
NDC: 59779-250 | Form: SOAP
Manufacturer: CVS Pharmacy
Category: otc | Type: HUMAN OTC DRUG LABEL
Date: 20111113

ACTIVE INGREDIENTS: SALICYLIC ACID 20 mg/1 mL
INACTIVE INGREDIENTS: WATER; LOW DENSITY POLYETHYLENE; PPG-15 STEARYL ETHER; GLYCERIN; STEARYL ALCOHOL; CETYL BETAINE; DISTEARYLDIMONIUM CHLORIDE; CETYL ALCOHOL; SODIUM LAURYL SULFATE; ALCOHOL; STEARETH-21; SODIUM CHLORIDE; DOCOSANOL; SYNTHETIC WAX (1200 MW); STEARETH-2; XANTHAN GUM; DIMETHYL PALMITAMINE; LAURYL ALCOHOL; CASEIN; MICROCRYSTALLINE WAX; METHYLCHLOROISOTHIAZOLINONE; EDETATE DISODIUM; ISOPROPYL ALCOHOL; BUTYLATED HYDROXYTOLUENE; DIPROPYLENE GLYCOL; PHENOXYETHANOL; SODIUM BENZOATE; ETHYLPARABEN; PROPYLPARABEN; FD&C BLUE NO. 1; SODIUM SULFATE

drug facts

Active ingredients Purpose
Salicylic Acid 2%............................................Acne Medication

Use
- for the treatment of acne

Keep out of reach of children. If swallowed, get medical help or contact
a Poison Control Center right away.

Use
- for the treatment of acne

Warnings
For external use only.
When using this product
- Avoid contact with eyes. If product gets into the eyes rinse thoroughly with water.
- with other topical acne medications at the same time or immediately following the use of this product,
increased dryness or irritation of the skin may occur. If this occurs, only one acne medication should
be used unless directed by a doctor.
- use only on the face and neck
Stop use and ask a doctor if skin or eye irritation develops.
Keep out of the reach of children. If swallowed, get medical help or contact a Poison Control Center right away

Directions
- Wet face
- dispense product generously and massage over face and neck
- rinse thoroughly and dry - for best results, use twice a day.
Other information
- Keep tightly closed
- Store in a cool dry place

Inactive Ingredients
behenyl alcohol, blue 1, butylated hydroxytoluene, cetyl alcohol,
cetyl betaine, dimethyl palmitamine, dipropylene glycol, disodium EDTA,
distearyldimonium chloride, ethylparaben, fragrance, glycerin, hydrolyzed milk protein,
isopropyl alcohol, layryl alcohol, magnesium chloride, magnesium nitrate,
methylchloroisothiazolinone, methylisothiazolinone, microcrystalline wax, phenoxyethanol,
PPG-15 stearyl ether, polyethylene, propylparaben, purified water, SD alcohol 40-B,
sodium benzoate, sodium chloride, sodium lauryl sulfate, sodium sulfate, steareth-2,
steareth-21, stearyl alcohol, syntheteic wax, xanthan gum